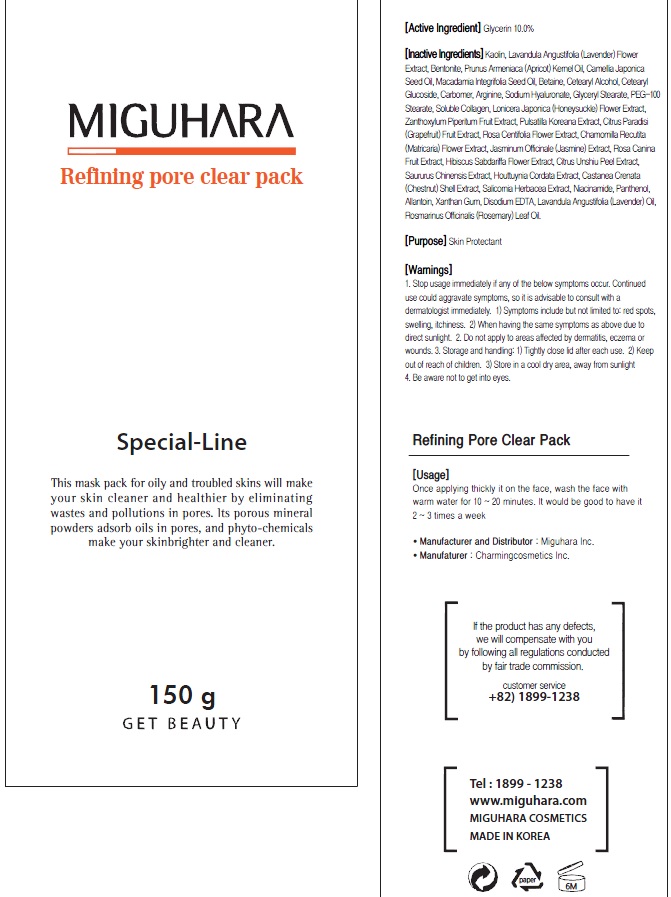 DRUG LABEL: Refining Pore Clear Pack
NDC: 70380-300 | Form: GEL
Manufacturer: MIGUHARA
Category: otc | Type: HUMAN OTC DRUG LABEL
Date: 20160224

ACTIVE INGREDIENTS: Glycerin 15 g/150 g
INACTIVE INGREDIENTS: Kaolin; LAVANDULA ANGUSTIFOLIA FLOWER

ACTIVE INGREDIENT

Active Ingredient: Glycerin 10.0%

INACTIVE INGREDIENT

Inactive Ingredients: Kaolin, Lavandula Angustifolia (Lavender) Flower Extract, Glycerin, Bentonite, Prunus Armeniaca (Apricot) Kernel Oil, Camellia Japonica Seed Oil, Macadamia Integrifolia Seed Oil, Betaine, Cetearyl Alcohol, Cetearyl Glucoside, Carbomer, Arginine, Sodium Hyaluronate, Glyceryl Stearate, PEG-100 Stearate, Soluble Collagen, Lonicera Japonica (Honeysuckle) Flower Extract, Zanthoxylum Piperitum Fruit Extract, Pulsatilla Koreana Extract, Citrus Paradisi (Grapefruit) Fruit Extract, Rosa Centifolia Flower Extract, Chamomilla Recutita (Matricaria) Flower Extract, Jasminum Officinale (Jasmine) Extract, Rosa Canina Fruit Extract, Hibiscus Sabdariffa Flower Extract, Citrus Unshiu Peel Extract, Saururus Chinensis Extract, Houttuynia Cordata Extract, Castanea Crenata (Chestnut) Shell Extract, Salicornia Herbacea Extract, Niacinamide, Panthenol, Allantoin, Xanthan Gum, Disodium EDTA, Lavandula Angustifolia (Lavender) Oil, Rosmarinus Officinalis (Rosemary) Leaf Oil

PURPOSE

Purpose: Skin Protectant

WARNINGS

1. Stop usage immediately if any of the below symptoms occur. Continued use could aggravate symptoms, so it is advisable to consult with a dermatologist immediately. 1) Symptoms include but not limited to: red spots, swelling, itchiness. 2) When having the same symptoms as above due to direct sunlight. 2. Do not apply to areas affected by dermatitis, eczema or wounds. 3. Storage and handling: 1) Tightly close lid after each use. 2 Keep out of reach of children 3) Store in a cool dry area, away from sunlight 4. Be aware not to get into eyes.

KEEP OUT OF REACH OF CHILDREN

Usage

Usage: Once applying thickly it on the face, wash the face with warm water for 10 ~ 20 minutes. It would be good to have it 2 ~ 3 times a week.

Usage

Usage: Once applying thickly it on the face, wash the face with warm water for 10 ~ 20 minutes. It would be good to have it 2 ~ 3 times a week.